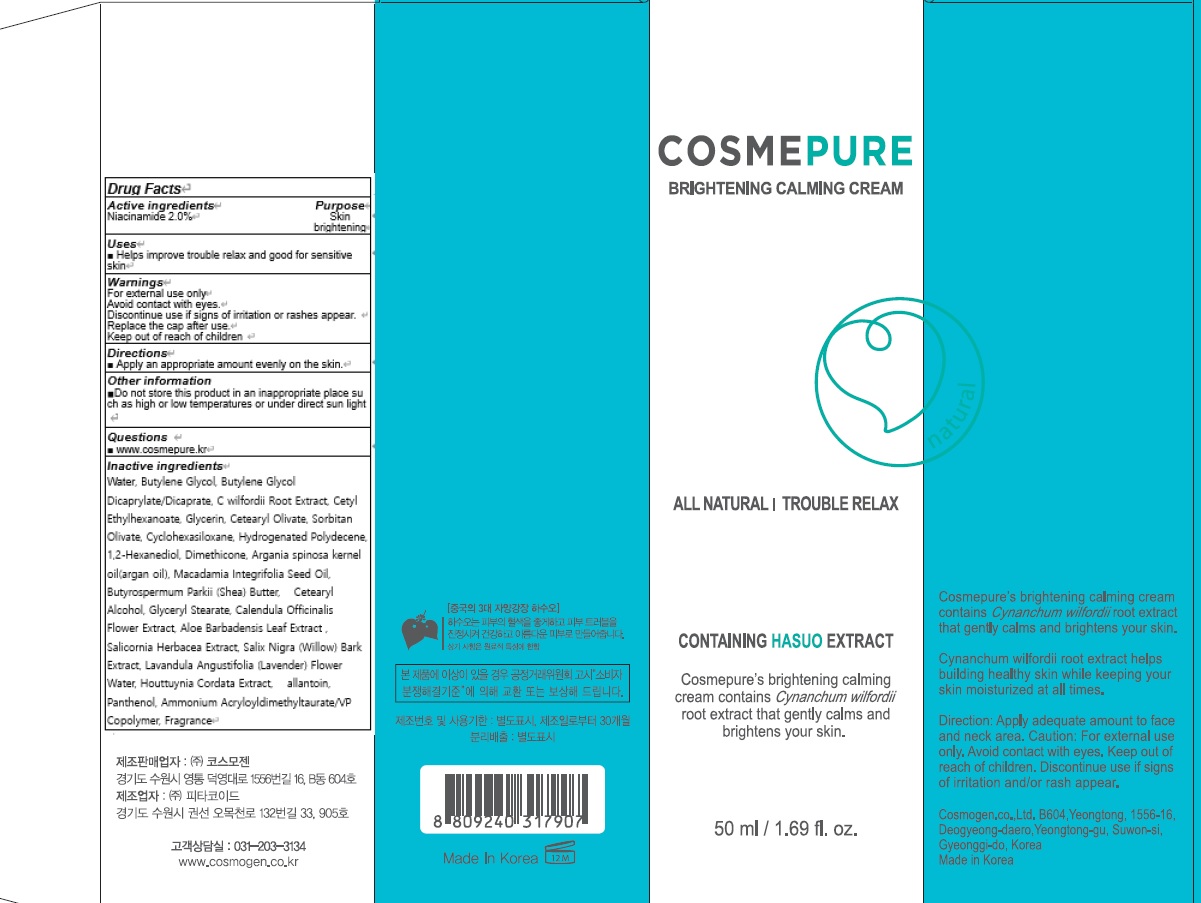 DRUG LABEL: COSMEPURE BRIGHTENING CALMING
NDC: 81418-010 | Form: CREAM
Manufacturer: Cosmogen Co., Ltd.
Category: otc | Type: HUMAN OTC DRUG LABEL
Date: 20210129

ACTIVE INGREDIENTS: Niacinamide 1.0 g/50 mL
INACTIVE INGREDIENTS: Water; Butylene Glycol

ACTIVE INGREDIENT

Niacinamide 2.0%

INACTIVE INGREDIENTS

Water, Butylene Glycol, Butylene Glycol Dicaprylate/Dicaprate, C wilfordii Root Extract, Cetyl Ethylhexanoate, Glycerin, Cetearyl Olivate, Sorbitan Olivate, Cyclohexasiloxane, Hydrogenated Polydecene, 1,2-Hexanediol, Dimethicone, Argania spinosa kernel oil(argan oil), Macadamia Integrifolia Seed Oil, Butyrospermum Parkii (Shea) Butter, Cetearyl Alcohol, Glyceryl Stearate, Calendula Officinalis Flower Extract, Aloe Barbadensis Leaf Extract , Salicornia Herbacea Extract, Salix Nigra (Willow) Bark Extract, Lavandula Angustifolia (Lavender) Flower Water, Houttuynia Cordata Extract, allantoin, Panthenol, Ammonium Acryloyldimethyltaurate/VP Copolymer, Fragrance

PURPOSE

Skin brigtening

WARNINGS

For external use only
Avoid contact with eyes.
Discontinue use if signs of irritation or rashes appear.
Replace the cap after use.
Keep out of reach of children

KEEP OUT OF REACH OF CHILDREN

Uses

■ Helps improve trouble relax and good for sensitive skin

Directions

■ Apply an appropriate amount evenly on the skin.

Other information

■ Do not store this product in an inappropriate place such as high or low temperatures or under direct sun light

QUESTIONS

■ www.cosmepure.kr